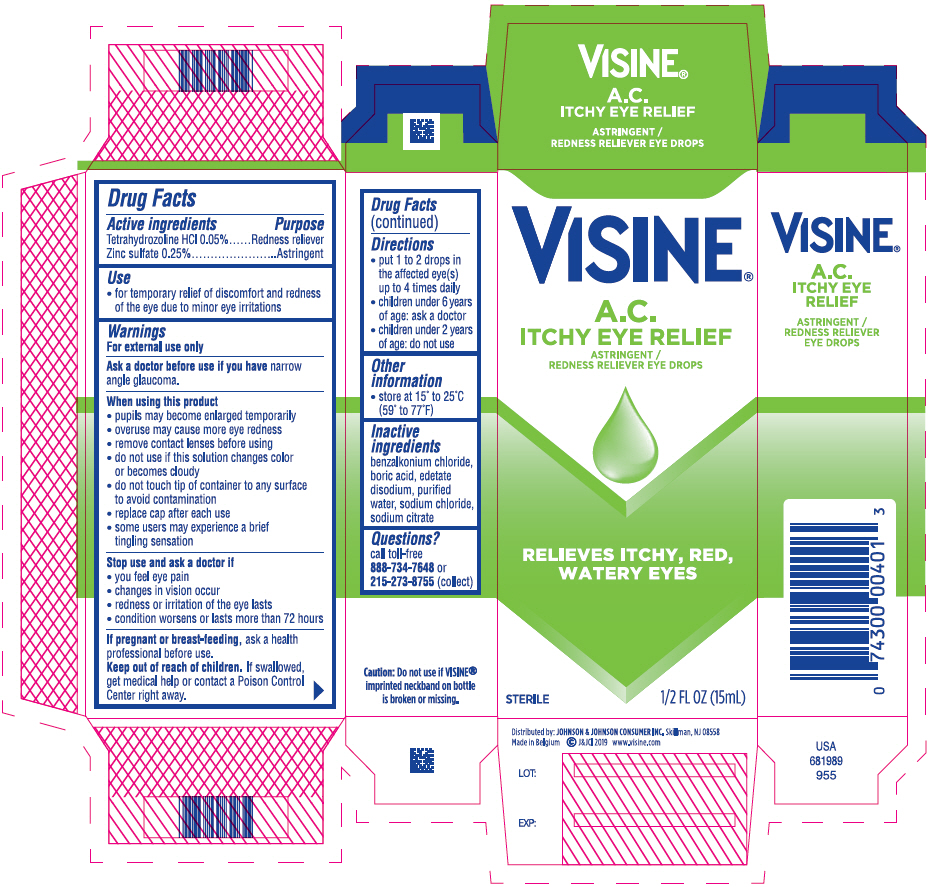 DRUG LABEL: Visine A.C. Itchy Eye Relief
NDC: 69968-0366 | Form: SOLUTION/ DROPS
Manufacturer: Kenvue Brands LLC
Category: otc | Type: HUMAN OTC DRUG LABEL
Date: 20241113

ACTIVE INGREDIENTS: TETRAHYDROZOLINE HYDROCHLORIDE 0.5 mg/1 mL; ZINC SULFATE, UNSPECIFIED FORM 2.5 mg/1 mL
INACTIVE INGREDIENTS: BENZALKONIUM CHLORIDE; BORIC ACID; EDETATE DISODIUM; WATER; SODIUM CHLORIDE; SODIUM CITRATE, UNSPECIFIED FORM

Visine® A.C. Itchy Eye Relief

Drug Facts

ACTIVE INGREDIENT

Active ingredients | Purpose
Tetrahydrozoline HCl 0.05% | Redness reliever
Zinc sulfate 0.25% | Astringent

Use

- for temporary relief of discomfort and redness of the eye due to minor eye irritations

Warnings

For external use only

Ask a doctor before use if you have narrow angle glaucoma.

When using this product

- pupils may become enlarged temporarily
- overuse may cause more eye redness
- remove contact lenses before using
- do not use if this solution changes color or becomes cloudy
- do not touch tip of container to any surface to avoid contamination
- replace cap after each use
- some users may experience a brief tingling sensation

Stop use and ask a doctor if

- you feel eye pain
- changes in vision occur
- redness or irritation of the eye lasts
- condition worsens or lasts more than 72 hours

PREGNANCY OR BREAST FEEDING

If pregnant or breast-feeding, ask a health professional before use.

Keep out of reach of children. If swallowed, get medical help or contact a Poison Control Center right away.

Directions

- put 1 to 2 drops in the affected eye(s) up to 4 times daily
- children under 6 years of age: ask a doctor
- children under 2 years of age: do not use

Other information

- store at 15° to 25°C (59° to 77°F)

Inactive ingredients

benzalkonium chloride, boric acid, edetate disodium, purified water, sodium chloride, sodium citrate

Questions?

call toll-free 888-734-7648 or 215-273-8755 (collect)

Distributed by: JOHNSON & JOHNSON CONSUMER INC. Skillman, NJ 08558

PRINCIPAL DISPLAY PANEL - 15 mL Bottle Carton

VISINE®

A.C.
ITCHY EYE RELIEF

ASTRINGENT /
REDNESS RELIEVER EYE DROPS

RELIEVES ITCHY, RED,
WATERY EYES

STERILE
1/2 FL OZ (15mL)